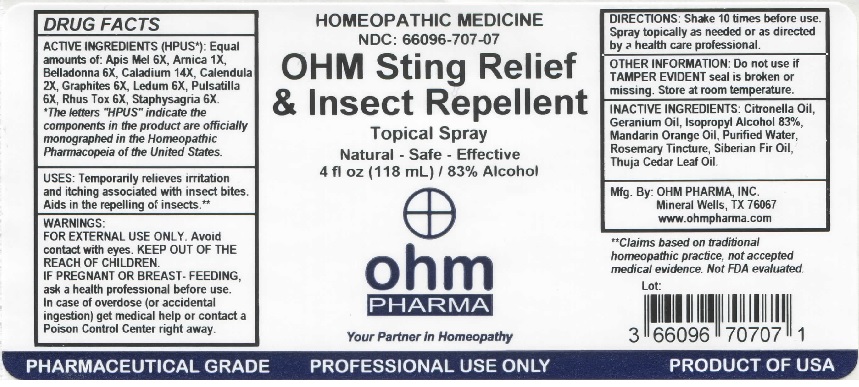 DRUG LABEL: OHM Sting Relief and Insect Repellent
NDC: 66096-707 | Form: SPRAY
Manufacturer: OHM PHARMA INC.
Category: homeopathic | Type: HUMAN OTC DRUG LABEL
Date: 20211229

ACTIVE INGREDIENTS: APIS MELLIFERA 6 [hp_X]/118 mL; ARNICA MONTANA 1 [hp_X]/118 mL; ATROPA BELLADONNA 6 [hp_X]/118 mL; DIEFFENBACHIA SEGUINE 14 [hp_X]/118 mL; CALENDULA ARVENSIS WHOLE 2 [hp_X]/118 mL; GRAPHITE 6 [hp_X]/118 mL; RHODODENDRON TOMENTOSUM LEAFY TWIG 6 [hp_X]/118 mL; ANEMONE PULSATILLA 6 [hp_X]/118 mL; TOXICODENDRON PUBESCENS LEAF 6 [hp_X]/118 mL; DELPHINIUM STAPHISAGRIA SEED 6 [hp_X]/118 mL
INACTIVE INGREDIENTS: CITRONELLA OIL; GERANIUM OIL, ALGERIAN TYPE; ISOPROPYL ALCOHOL; MANDARIN OIL; WATER; ROSEMARY; ABIES SIBIRICA LEAF OIL; CEDAR LEAF OIL

OHM Sting Relief & Insect Repellent

ACTIVE INGREDIENT

ACTIVE INGREDIENTS (HPUS*): Equal amounts of: Apis Mel 6X, Arnica 1X, Belladonna 6X, Caladium 14X, Calendula 2X, Graphites 6X, Ledum 6X, Pulsatilla 6X, Rhus Tox 6X, Staphysagria 6X.

*The letters "HPUS" indicate the components in the product are officially monographed in the Homeopathic Pharmacopeia of the United States.

INDICATIONS AND USAGE

USES: Temporarily relieves irritation and itching associated with insect bites. Aids in the repelling of insects.**

**Claims based on traditional homeopathic practice, not accepted medical evidence. Not FDA evaluated.

WARNINGS

WARNINGS: FOR EXTERNAL USE ONLY. Avoid contact with eyes. IF PREGNANT OR BREAST-FEEDING, ask a health professional before use. In case of overdose (or accidental ingestion) get medical help or contact a Poison Control Center right away.

- KEEP OUT OF REACH OF CHILDREN.

DOSAGE AND ADMINISTRATION

DIRECTIONS: Shake 10 times before use. Spray topically as needed or as directed by a health care professional.

OTHER INFORMATION: Do not use if TAMPER EVIDENT seal is broken or missing. Store at room temperature.

INACTIVE INGREDIENT

INACTIVE INGREDIENTS: Citronella Oil, Geranium Oil, Isopropyl Alcohol 83%, Mandarin Orange Oil, Purified Water, Rosemary Tincture, Siberian Fir Oil, Thuja Cedar Leaf Oil.

QUESTIONS

Mfg. By: OHM PHARMA, INC. Mineral Wells, TX 76067

www.ohmpharma.com

PACKAGE LABEL

HOMEOPATHIC MEDICINE

NDC: 66096-707-07

OHM Sting Relief

& Insect Repellent

Topical Spray

Natural - Safe - Effective

4 fl oz (118 mL) / 83% Alcohol

PURPOSE

Irritation and itching associated with insect bites. Aids in the repelling of insects.